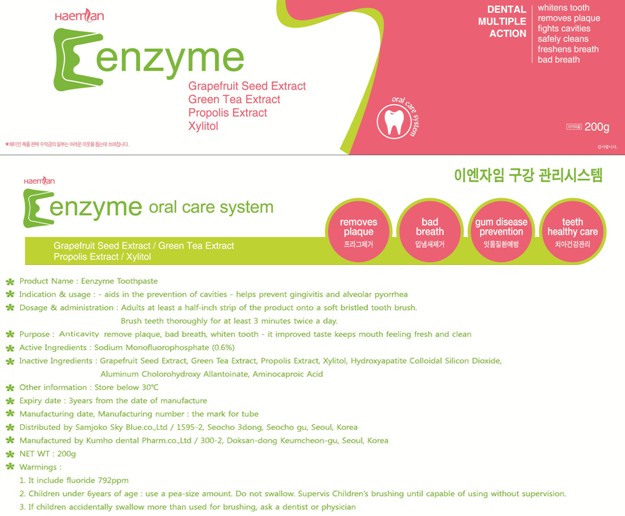 DRUG LABEL: E ENZYME
NDC: 76414-010 | Form: PASTE, DENTIFRICE
Manufacturer: SAMJOKO SKYBLUE CO., LTD.
Category: otc | Type: HUMAN OTC DRUG LABEL
Date: 20111114

ACTIVE INGREDIENTS: SODIUM MONOFLUOROPHOSPHATE 1.2 g/200 g
INACTIVE INGREDIENTS: Water; ATTAPULGITE; XYLITOL; GLYCERIN; GRAPEFRUIT SEED OIL; GREEN TEA LEAF; PROPOLIS WAX

Drug Facts

Active ingredient: SODIUM MONOFLUOROPHOSPHATE 0.6%

Inactive ingredients:

Water, D-Sorbitol Liquefied, Colloidal Silcon Dioxide, ATTAPULGITE, PEG-1500, Sluminum chlorohydroxg allautonate, Aminocaparoid Acid, Sodium Saccharine, XYLITOL, Butyl-P oxybenzoare, Hydroxyapatite, Carbon hydrozen Sodium, GLYCERIN, Carboxymethylcellulose nattrium, Sulfuricacid, GRAPEFRUIT SEED OIL, GREEN TEA LEAF, PROPOLIS WAX, I-mentol, Optimint

PURPOSE

Purpose: Anticavity, remove plaque, bad breath, whiten tooth - it improved taste keeps mouth feeling fresh and clean.

Warnings:
It includes fluoride 792ppm
Children under 6 years of age: use a pea-size amount. Do not swallow. Supervis children's brushing until capable of using without supervision.
If children accidentally swallow more than used for brushing, ask a dentist or physician.

Keep out of reach of children:

Keep out of reach of children.

Indication and usage:
Aids in the prevention of cavities
Helps prevent gingivitis and alveolar pyorrhea

Dosage and administration:
Adults at least a half-inch strip of the product onto a soft bristled tooth brush.
Brush teeth thoroughly for at least 3 minutes twice a day.